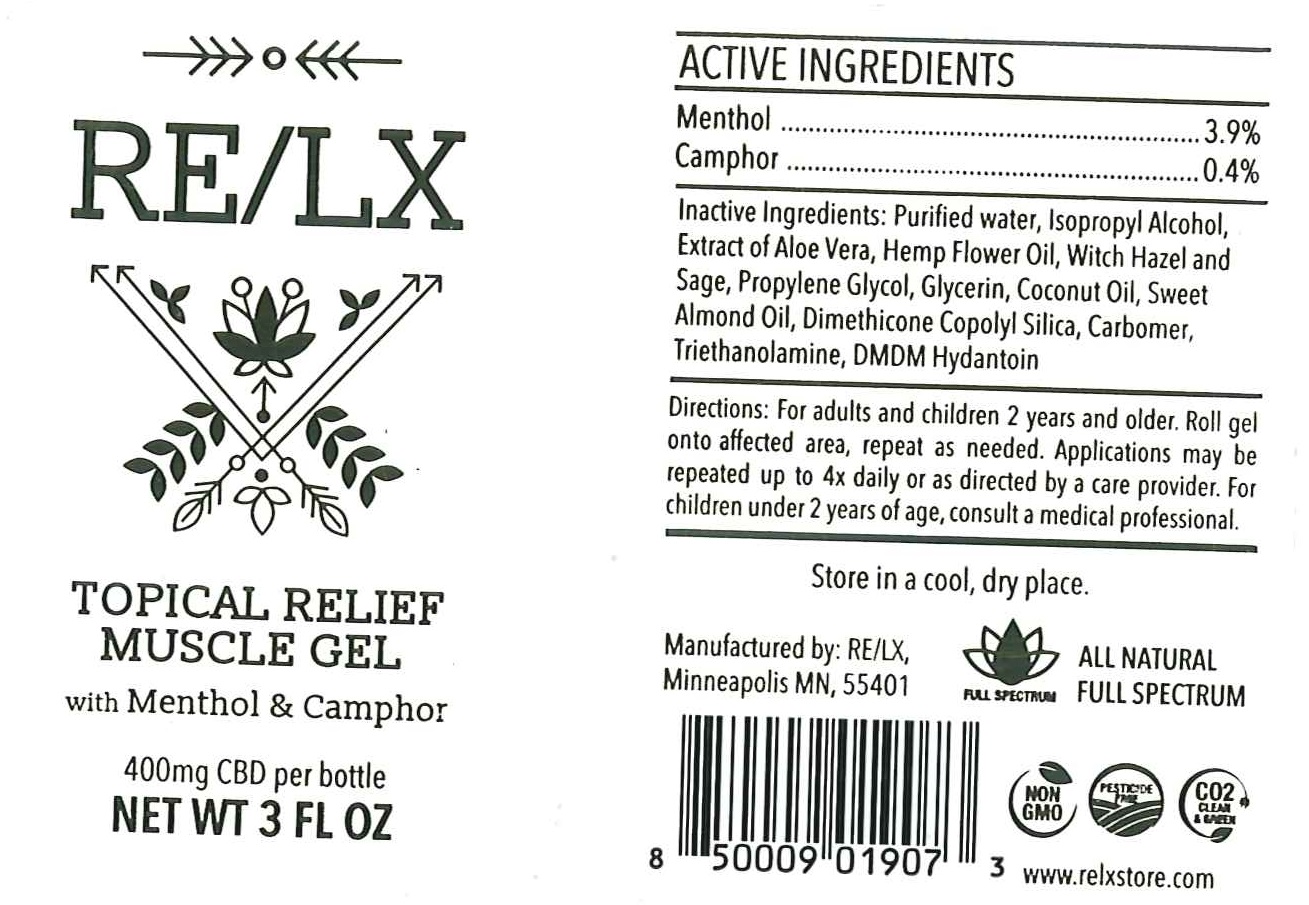 DRUG LABEL: TOTAL MUSCLE RELIEF
NDC: 73278-101 | Form: GEL
Manufacturer: Nemadji Management LLC
Category: otc | Type: HUMAN OTC DRUG LABEL
Date: 20190802

ACTIVE INGREDIENTS: MENTHOL 3.9 g/100 mL; CAMPHOR OIL 0.4 g/100 mL
INACTIVE INGREDIENTS: WATER; ISOPROPYL ALCOHOL; ALOE VERA LEAF; HEMP; WITCH HAZEL; SAGE; PROPYLENE GLYCOL; GLYCERIN; COCONUT OIL; CARBOMER HOMOPOLYMER TYPE C (ALLYL PENTAERYTHRITOL CROSSLINKED); ALMOND OIL; PEG/PPG-18/18 DIMETHICONE; DMDM HYDANTOIN; TROLAMINE

ACTIVE INGREDIENTS

MENTHOL 3.9%

cAMPHOR 0.4%

PURPOSE

TOPICAL ANALGESIC

WARNINGS

EXTERNAL USE ONLY

KEEP OUT OF REACH OF CHILDREN.

USES

TOPICAL RELIEF MUSCLE GEL

DIRECTIONS

FOR ADULTS AND CHILDREN 2 YEARS AND OLDER. ROLL GEL ONTO AFFECTED AREA, REPEAT AS NEEDED. APPLICATIONS MAY BE REPEATED UP TO 4X DAILY OR AS DIRECTED BY A CARE PROVIDER. FOR CHILDREN UNDER 2 YEARS OF AGE, CONSULT A MEDICAL PROFESSIONAL.

INACTIVE INGREDIENTS

PURIFIED WATER, ISOPROPYL ALCOHOL, EXTRACT OF ALOE VERA, HEMP GLOWER OIL, WITCH HAZEL AND SAGE, PROPYLENE GLYCOL, GLYCERIN, COCONUT OIL, SWEET ALMOND OIL, DIMETHICONE COPOLYOL SILICA, CARBOMER, TRIETHANOLAMINE, DMDM HYDANTOIN